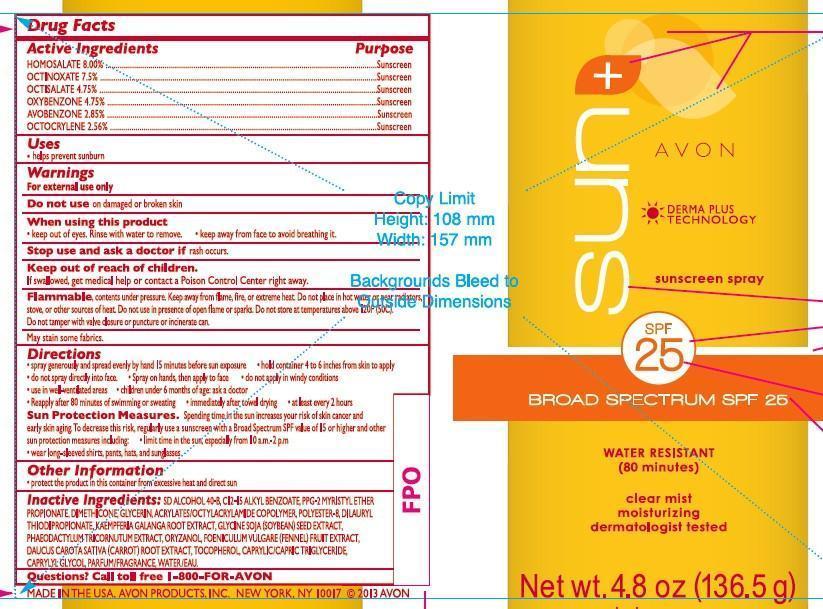 DRUG LABEL: Avon Sun
NDC: 10096-0296 | Form: AEROSOL, SPRAY
Manufacturer: New Avon LLC
Category: otc | Type: HUMAN OTC DRUG LABEL
Date: 20160217

ACTIVE INGREDIENTS: HOMOSALATE 80 mg/1 g; OCTINOXATE 75 mg/1 g; OCTISALATE 47.5 mg/1 g; OXYBENZONE 47.5 mg/1 g; AVOBENZONE 28.5 mg/1 g; OCTOCRYLENE 25.6 mg/1 g

Active ingredients
HOMOSALATE 8.00%..................

OCTINOXATE 7.5%.....................

OCTISALATE 4.75%.....................

OXYBENZONE 4.75%.....................

AVOBENZONE 2.85%...................

OCTOCRYLENE 2.56%..................

Purpose
.................................Sunscreen

.................................Sunscreen

.................................Sunscreen

.................................Sunscreen

.................................Sunscreen

.................................Sunscreen

Uses
• helps prevent sunburn

Warnings
For external use only

Do not use on damaged or broken skin

When using this product

- keep out of eyes. Rinse with water to remove.
- keep away from face to avoid breathing it.

Stop use and ask a doctor if rash occurs

Keep out of reach of children.

If swallowed, get medical help or contact a Poison Control Center right away.

GENERAL PRECAUTIONS

Flammable, contents under pressure. Keep away from flame, fire or extreme heat. Do not place in hot water or near radiators, stove, or other sources of heat. Do not use in presence of open flame or sparks. Do not store at temparatures above 120F (50C). Do not tamper with valve closure or puncture or incinerate can.

Directions
• spray generously and spread evenly by hand 15 minutes before sun exposure

• hold container 4 to 6 inches from skin to apply

• do not spray directly into face

• Spray on hands, then apply to face

• do not apply in windy conditions

• use in well-ventilated areas
• children under 6 months of age: ask a doctor

• Reapply after 80 minutes of swimming or sweating

• immediately after towel drying

• at least every 2 hours

• Sun Protection Measures. Spending time in the sun increases your risk of skin cancer and early skin aging. To decrease this risk, regularly use a sunscreen with a Broad Spectrum SPF value of 15 or higher and other sun protection measures including:

• limit time in the sun, especially from 10 a.m. – 2 p.m.
• wear long-sleeved shirts, pants, hats, and sunglasses

Other information

• protect the product in this container from excessive heat and direct sun

Inactive Ingredients:
SD ALCOHOL 40-B, C12-15 ALKYL BENZOATE, PPG-2 MYRISTYL ETHER PROPIONATE, DIMETHICONE, GLYCERIN, ACRYLATES/OCTYLACRYLAMIDE COPOLYMER, POLYESTER-8, DILAURYL THIODIPROPIONATE, KAEMPFERIA GALANGA ROOT EXTRACT, GLYCINE SOJA (SOYBEAN) SEED EXTRACT,
PHAEODACTYLUM TRICORNUTUM EXTRACT, ORYZANOL, FOENICULUM VULGARE (FENNEL) FRUIT EXTRACT, DAUCUS CAROTA SATIVA (CARROT) ROOT EXTRACT, TOCOPHEROL, CAPRYLIC/CAPRIC TRIGLYCERIDE, CAPRYLYL GLYCOL, PARFUM/FRAGRANCE, WATER/EAU

Questions?
Call toll free 1-800-FOR-AVON